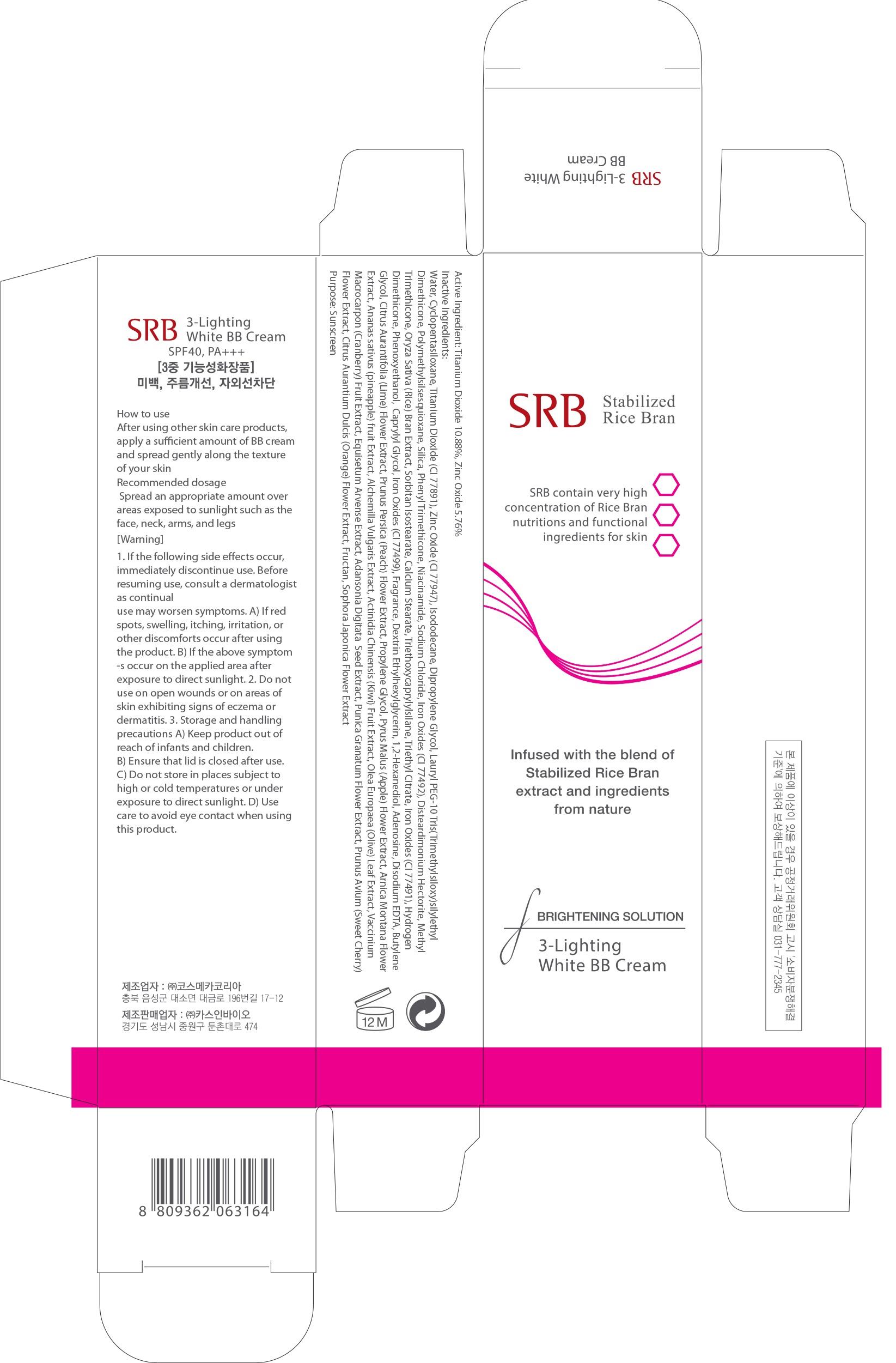 DRUG LABEL: SRB 3 Lighting White BB
NDC: 70218-020 | Form: CREAM
Manufacturer: CASINBIO CO., LTD.
Category: otc | Type: HUMAN OTC DRUG LABEL
Date: 20151112

ACTIVE INGREDIENTS: Titanium Dioxide 3.80 g/35 g; Zinc Oxide 2.01 g/35 g
INACTIVE INGREDIENTS: Water; Isododecane

ACTIVE INGREDIENT

Active Ingredient: Titanium Dioxide 10.88%, Zinc Oxide 5.76%

INACTIVE INGREDIENT

Inactive Ingredients: Water, Cyclopentasiloxane, Isododecane, Dipropylene Glycol, Lauryl PEG-10 Tris(Trimethylsiloxy)silylethyl Dimethicone, Polymethylsilsesquioxane, Silica, Phenyl Trimethicone, Niacinamide, Sodium Chloride, Iron Oxides (CI 77492), Disteardimonium Hectorite, Methyl Trimethicone, Oryza Sativa (Rice) Bran Extract, Sorbitan Isostearate, Calcium Stearate, Triethoxycaprylylsilane, Triethyl Citrate, Iron Oxides (CI 77491), Hydrogen Dimethicone, Phenoxyethanol, Caprylyl Glycol, Iron Oxides (CI 77499), Fragrance, Dextrin Ethylhexylglycerin, 1,2-Hexanediol, Adenosine, Disodium EDTA, Butylene Glycol, Citrus Aurantifolia (Lime) Flower Extract, Prunus Persica (Peach) Flower Extract, Propylene Glycol, Pyrus Malus (Apple) Flower Extract, Arnica Montana Flower Extract, Ananas sativus (pineapple) fruit Extract, Alchemilla Vulgaris Extract, Actinidia Chinensis (Kiwi) Fruit Extract, Olea Europaea (Olive) Leaf Extract, Vaccinium Macrocarpon (Cranberry) Fruit Extract, Equisetum Arvense Extract, Adansonia Digitata Seed Extract, Punica Granatum Flower Extract, Prunus Avium (Sweet Cherry) Flower Extract, Citrus Aurantium Dulcis (Orange) Flower Extract, Fructan, Sophora Japonica Flower Extract

PURPOSE

Purpose: Sunscreen

WARNINGS

Warnings: 1. If the following side effects occur, immediately discontinue use. Before resuming use, consult a dermatologist as continual use may worsen symptoms. A) If red spots, swelling, itching, irritation, or other discomforts occur after using the product. B) If the above symptoms occur on the applied area after exposure to direct sunlight. 2. Do not use on open wounds or on areas of skin exhibiting signs of eczema or dermatitis. 3. Storage and handling precautions A) Keep product out of reach of infants and children. B) Ensure that lid is closed after use. C) Do not store in places subject to high or cold temperatures or under exposure to direct sunlight. D) Use care to avoid eye contact when using this product.

DESCRIPTION

How to use: Apply an appropriate amount to areas exposed to sunlight such as the face, neck, arms, legs, and spread evenly.

Recommended dosage: Spread an appropriate amount over areas exposed to sunlight such as the face, neck, arms, and legs